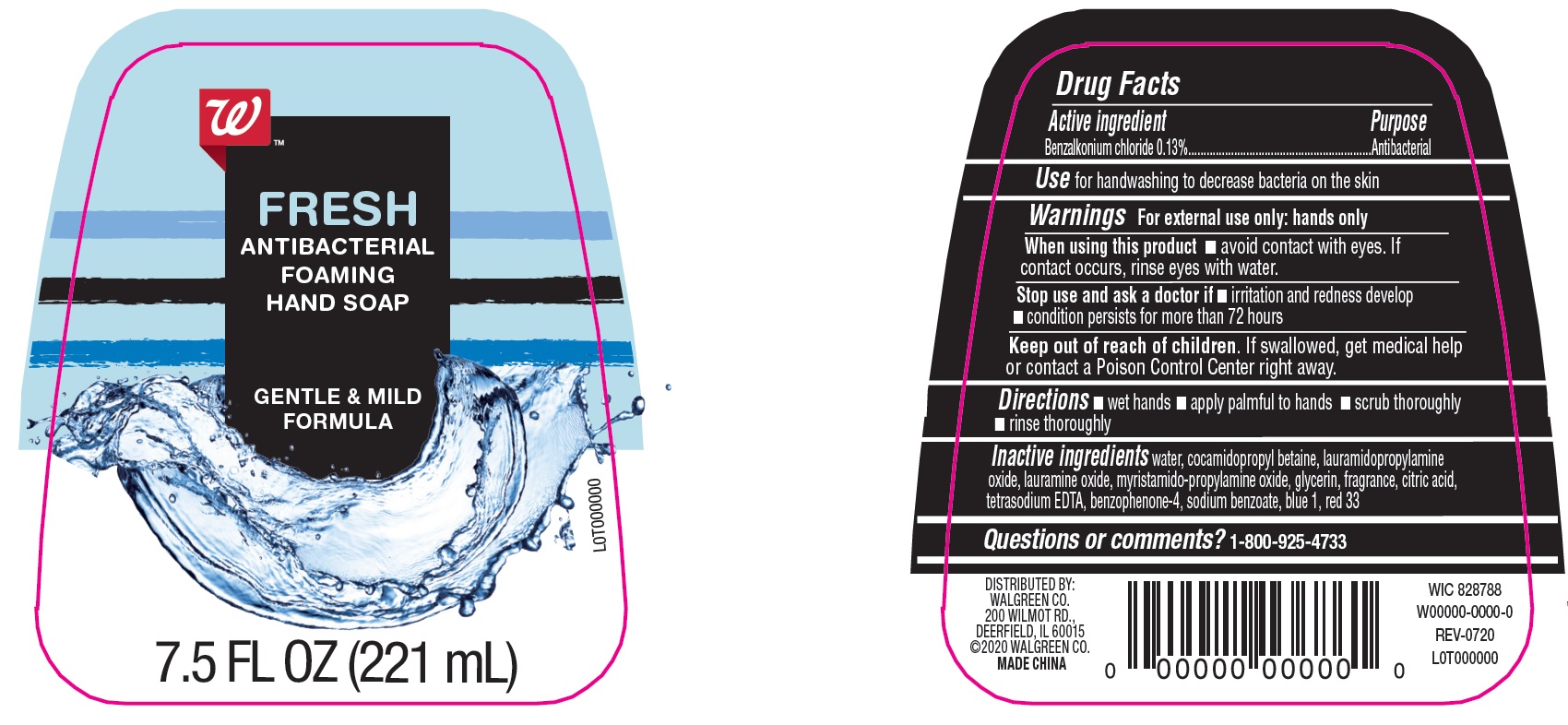 DRUG LABEL: Walgreens Fresh Antibacterial Foaming Hand
NDC: 0363-9000 | Form: SOAP
Manufacturer: Walgreen Company
Category: otc | Type: HUMAN OTC DRUG LABEL
Date: 20200810

ACTIVE INGREDIENTS: BENZALKONIUM CHLORIDE 1.3 mg/1 mL
INACTIVE INGREDIENTS: WATER; LAURAMIDOPROPYLAMINE OXIDE; LAURAMINE OXIDE; CITRIC ACID MONOHYDRATE; SULISOBENZONE; COCAMIDOPROPYL BETAINE; MYRISTAMIDOPROPYLAMINE OXIDE; GLYCERIN; EDETATE SODIUM; SODIUM BENZOATE; FD&C BLUE NO. 1; D&C RED NO. 33

Walgreens Fresh Antibacterial Foaming Hand Saop

Active ingredient

Benzalkonium Chloride 0.13%

Purpose

Antibacterial

Use

for handwashing to decrease bacteria on the skin

Warnings

For external use only: hands only

When using this product

- avoid contact with eyes. If contact occurs, rinse eyes with water.

Stop use and ask a doctor if

- irritation and redness develop
- condition persists for more than 72 hours

Keep out of reach of children.

If swallowed get medical help or contact a Poison Control Center right away.

Directions

- wet hands
- apply palmful to hands
- scrub thoroughly
- rinse thoroughly

Inactive ingredients

water, cocamidopropyl betaine, lauramidopropylamine oxide, lauramine oxide, myristamido-propylamine oxide, glycerin, fragrance, citric acid, tetrasodium EDTA, benzophenone-4, sodium benzoate, blue 1, red 33

Questions or comments?

1-800-925-4733

Company Information

DISTRIBUTED BY:

WALGREEN CO.

200 WILMOT RD.

DEERFIELD, IL 60015

Product Packaging

FRESH

ANTIBACTERIAL

FOAMING

HAND SOAP

GENTLE & MILD

FORMULA

7.5 FL OZ (221 mL)